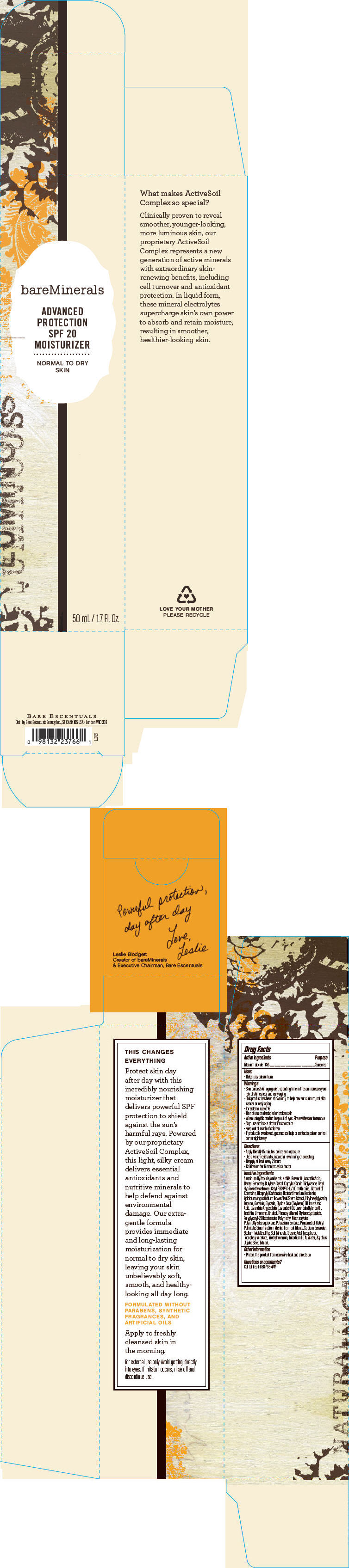 DRUG LABEL: bareMinerals Advanced Protection SPF 20 Moisturizer
NDC: 98132-722 | Form: LOTION
Manufacturer: Bare Escentuals Beauty, Inc.
Category: otc | Type: HUMAN OTC DRUG LABEL
Date: 20181218

ACTIVE INGREDIENTS: TITANIUM DIOXIDE 60 mg/1 mL
INACTIVE INGREDIENTS: ALUMINUM HYDROXIDE; CHAMAEMELUM NOBILE FLOWER OIL; ASCORBIC ACID; BENZYL BENZOATE; BUTYLENE GLYCOL; MEDIUM-CHAIN TRIGLYCERIDES; .BETA.-CITRONELLOL, (R)-; COUMARIN; DICAPRYLYL CARBONATE; DISTEARDIMONIUM HECTORITE; EPILOBIUM ANGUSTIFOLIUM FLOWERING TOP; ETHYLHEXYLGLYCERIN; EUGENOL; GERANIOL; GLYCERIN; SOYBEAN OIL; ISOSTEARIC ACID; LAVENDER OIL; LAVANDIN OIL; LINALOOL, (+/-)-; PHENOXYETHANOL; POLYGLYCERYL-2 DIISOSTEARATE; POTASSIUM SORBATE; PROPANEDIOL; VITAMIN A PALMITATE; SODIUM BENZOATE; SODIUM METABISULFITE; STEARIC ACID; TOCOPHEROL; .ALPHA.-TOCOPHEROL ACETATE; TRIETHYLHEXANOIN; EDETATE TRISODIUM; WATER; JUJUBE SEED

bareMinerals Advanced Protection SPF 20 Moisturizer
Normal to Dry Skin

Drug Facts

Active ingredients

Titanium dioxide 6%

Purpose

Sunscreen

Uses

- Helps prevent sunburn

Warnings

- Skin cancer/skin aging alert: spending time in the sun increases your risk of skin cancer and early aging
- This product has been shown only to help prevent sunburn, not skin cancer or early aging
- For external use only

- Do not use on damaged or broken skin

- When using this product keep out of eyes. Rinse with water to remove

- Stop use and ask a doctor if rash occurs

- Keep out of reach of children
- If product is swallowed, get medical help or contact a poison control center right away

Directions

- Apply liberally 15 minutes before sun exposure
- Use a water resistant sunscreen if swimming or sweating
- Reapply at least every 2 hours
- Children under 6 months: ask a doctor

Inactive ingredients

Aluminum Hydroxide, Anthemis Nobilis Flower Oil, Ascorbic Acid, Benzyl Benzoate, Butylene Glycol, Caprylic/Capric Triglyceride, Cetyl Hydroxyethylcellulose, Cetyl PEG/PPG-10/1 Dimethicone, Citronellol, Coumarin, Dicaprylyl Carbonate, Disteardimonium Hectorite, Epilobium Angustifolium Flower/Leaf/Stem Extract, Ethylhexylglycerin, Eugenol, Geraniol, Glycerin, Glycine Soja (Soybean) Oil, Isostearic Acid, Lavandula Angustifolia (Lavender) Oil, Lavandula Hybrida Oil, Lecithin, Limonene, Linalool, Phenoxyethanol, Phytoecdysteroids, Polyglyceryl-2 Diisostearate, Polymethyl Methacrylate, Polymethylsilsesquioxane, Potassium Sorbate, Propanediol, Retinyl Palmitate, Sinorhizobium Meliloti Ferment Filtrate, Sodium Benzoate, Sodium Metabisulfite, Soil Minerals, Stearic Acid, Tocopherol, Tocopheryl Acetate, Triethylhexanoin, Trisodium EDTA, Water, Zizyphus Jujuba Seed Extract.

Other information

- Protect this product from excessive heat and direct sun

Questions or comments?

Call toll free 1-888-795-4747

Dist. by Bare Escentuals Beauty, Inc., SF, CA 94105 USA

PRINCIPAL DISPLAY PANEL - 50 mL Bottle Box

bareMinerals

ADVANCED
PROTECTION
SPF 20
MOISTURIZER

NORMAL TO DRY
SKIN

50 mL / 1.7 Fl. Oz.